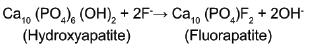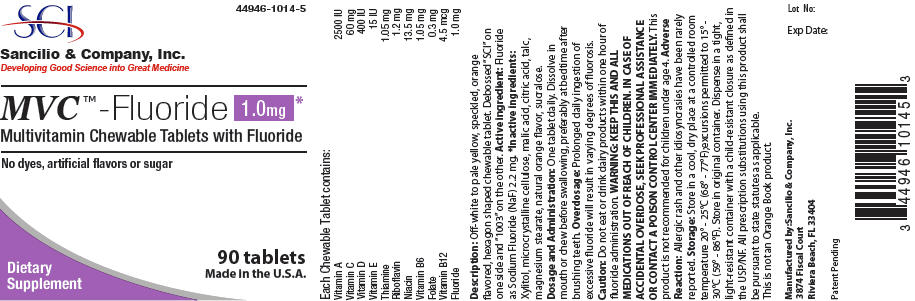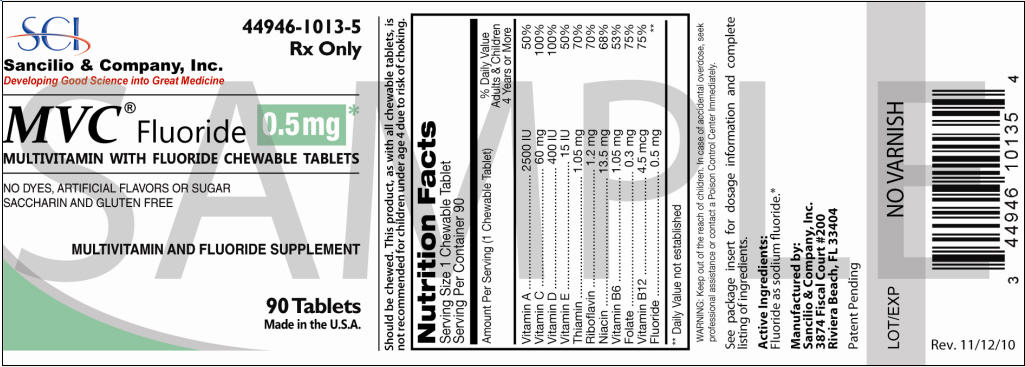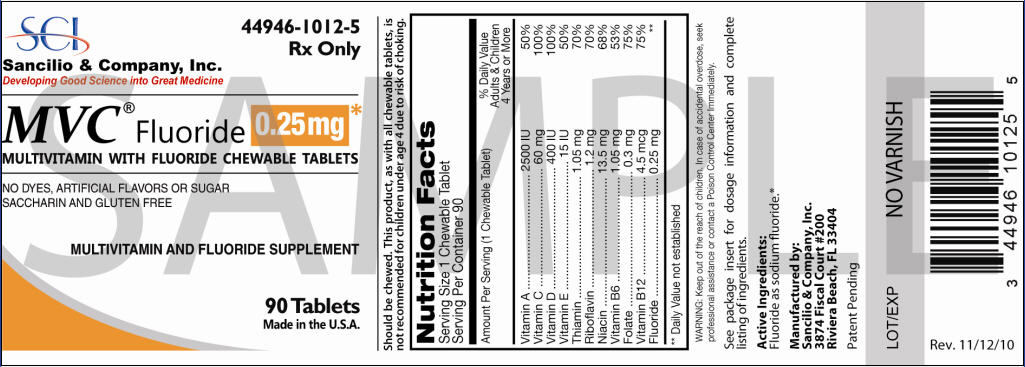 DRUG LABEL: MVC
NDC: 44946-1014 | Form: TABLET, CHEWABLE
Manufacturer: Sancilio & Company Inc
Category: other | Type: DIETARY SUPPLEMENT
Date: 20180226

ACTIVE INGREDIENTS: Sodium Fluoride 1 mg/1 1; Vitamin A Palmitate 2500 [iU]/1 1; Ascorbic Acid 60 mg/1 1; Cholecalciferol 400 [iU]/1 1; .Alpha.-Tocopherol Acetate 15 [iU]/1 1; Thiamine Mononitrate 1.05 mg/1 1; Riboflavin 1.2 mg/1 1; Niacinamide 13.5 mg/1 1; Pyridoxine Hydrochloride 1.05 mg/1 1; Folic Acid 0.3 mg/1 1; cyanocobalamin 4.5 ug/1 1
INACTIVE INGREDIENTS: Citric Acid Monohydrate; Malic Acid; Microcrystalline Cellulose; Sucralose; Xylitol; Talc; Magnesium Stearate

MULTIVITAMIN WITH FLUORIDE
CHEWABLE TABLETS

HEALTH CLAIM

Rx only

STATEMENT OF IDENTITY

Nutrition Facts
Serving Size 1 Chewable Tablet
Serving Per Container 30 or 90
Amount Per Serving (1 Chewable Tablet) | 1.0 mg | 0.5 mg | 0.25 mg | %DV Adults & Children 4 Years or More
Vitamin A | 2500 IU | 2500 IU | 2500 IU | 50%
Vitamin C | 60 mg | 60 mg | 60 mg | 100%
Vitamin D | 400 IU | 400 IU | 400 IU | 100%
Vitamin E | 15 IU | 15 IU | 15 IU | 50%
Thiamin | 1.05 mg | 1.05 mg | 1.05 mg | 70%
Riboflavin | 1.2 mg | 1.2 mg | 1.2 mg | 70%
Niacin | 13.5 mg | 13.5 mg | 13.5 mg | 68%
Vitamin B6 | 1.05 mg | 1.05 mg | 1.05 mg | 53%
Folate | 0.3 mg | 0.3 mg | 0.3 mg | 75%
Vitamin B12 | 4.5 mcg | 4.5 mcg | 4.5 mcg | 75%
Fluoride | 1.0 mg | 0.5 mg | 0.25 mg | [Daily Value (%DV) not established]

Active ingredients

Fluoride as sodium fluoride.

Other Ingredients

Xylitol, microcrystalline cellulose, mannitol, talc, magnesium stearate, sucralose, natural flavors, citric acid.

CLINICAL PHARMACOLOGY

It is well established that fluoridation of the water supply (1 ppm fluoride) during the period of tooth development leads to a significant decrease in the incidence of dental caries.

Multivitamin with Fluoride Chewable Tablets provide sodium fluoride and ten essential vitamins in a chewable tablet. Because the tablets are chewable, they provide a topical as well as systemic source of fluoride.

Hydroxyapatite is the principal crystal for all calcified tissue in the human body. The fluoride ion reacts with the hydroxyapatite in the tooth as it forms to produce the more caries-resistant crystal, fluorapatite. The reaction may be expressed by the equation:

Three stages of fluoride deposition in tooth enamel can be distinguished:

1. Small amounts (reflecting the low levels of fluoride in tissue fluids) are incorporated into the enamel crystals while they are being formed.
2. After enamel has been laid down, fluoride deposition continues in the surface enamel. Diffusion of fluoride from the surface inward is apparently restricted.
3. After eruption, the surface enamel acquires fluoride from the water, food, supplementary fluoride and smaller amounts from saliva.

INDICATIONS AND USAGE

Supplementation of the diet with fluoride and ten essential vitamins.

Multivitamin with 1.0 mg Fluoride Chewable Tablets provide fluoride in tablet form for children 6-16 years of age in areas where the water fluoride level is less than 0.3 ppm.

Multivitamin with 0.5 mg Fluoride Chewable Tablets provide fluoride in tablet form for children 4-6 years of age where the water fluoride level is less than 0.3 ppm, and for children 6 years of age and above where the drinking water contains 0.3 through 0.6 ppm of fluoride.

Multivitamin with 0.25 mg Fluoride Chewable Tablets provide fluoride in tablet form for children 4-6 years of age where the drinking water contains 0.3 through 0.6 ppm of fluoride.

Multivitamin with Fluoride Chewable Tablets supply significant amounts of vitamins A, C, D, E, thiamin, riboflavin, niacin, vitamin B6, vitamin B12, and folate to supplement the diet, and to help assure that nutritional deficiencies of these vitamins will not develop.

The American Academy of Pediatrics recommends that children up to age 16, in areas where drinking water contains less than optimal levels of fluoride, receive daily fluoride supplementation.

Children using Multivitamin with Fluoride Chewable Tablets regularly should receive semiannual dental examinations. The regular brushing of teeth and attention to good oral hygiene practices are also essential.

WARNING

Keep this and all medication out of the reach of children. In case of accidental overdose, seek professional assistance or contact a poison control center immediately.

Should be chewed. This product, as with all chewable tablets, is not recommended for children under age 4 due to risk of choking.

PRECAUTIONS

The suggested dose of Multivitamin with Fluoride Chewable Tablets should not be exceeded, since dental fluorosis may result from continued ingestion of large amounts of fluoride.

Before prescribing Multivitamin with Fluoride Chewable Tablets:

1. Determine the fluoride content of the drinking water from all major sources.
2. Make sure the child is not receiving significant amounts of fluoride from other sources such as medications and swallowed toothpaste.
3. Periodically check to make sure that the child does not develop significant dental fluorosis.

ADVERSE REACTIONS

Allergic rash and other idiosyncrasies have been rarely reported.

DOSAGE AND ADMINISTRATION

One tablet daily or as prescribed.

HOW SUPPLIED

Multivitamin with 1.0 mg, 0.5 mg and 0.25 mg Fluoride Chewable Tablets are all available in 30 and 90 tablet bottles.

STORAGE

Store in a cool dry place. Protect from light and moisture.

HEALTH CLAIM

Manufactured by:
Sancilio & Company, Inc.
3874 Fiscal Court #200
Riviera Beach, FL 33404

PRINCIPAL DISPLAY PANEL - 1.0 mg Bottle Label

44946-1014-5

SCI
Sancilio & Company, Inc.
Developing Good Science into Great Medicine

MVC ™-Fluoride 1.0mg*
Multivitamin Chewable Tablets with Fluoride

No dyes, artificial flavors or sugar

Dietary
Supplement

90 tablets
Made in the U.S.A.

PRINCIPAL DISPLAY PANEL - 0.5mg Bottle Label

SCI
Sancilio & Company, Inc.
Developing Good Science into Great Medicine

44946-1013-5
Rx Only

MVC® Fluoride
0.5mg *
MULTIVITAMIN WITH FLUORIDE CHEWABLE TABLETS

NO DYES, ARTIFICIAL FLAVORS OR SUGAR
SACCHARIN AND GLUTEN FREE

MULTIVITAMIN AND FLUORIDE SUPPLEMENT

90 Tablets
Made in the U.S.A.

PRINCIPAL DISPLAY PANEL - 0.25mg Bottle Label

SCI
Sancilio & Company, Inc.
Developing Good Science into Great Medicine

44946-1012-5
Rx Only

MVC® Fluoride
0.25mg *
MULTIVITAMIN WITH FLUORIDE CHEWABLE TABLETS

NO DYES, ARTIFICIAL FLAVORS OR SUGAR
SACCHARIN AND GLUTEN FREE

MULTIVITAMIN AND FLUORIDE SUPPLEMENT

90 Tablets
Made in the U.S.A.